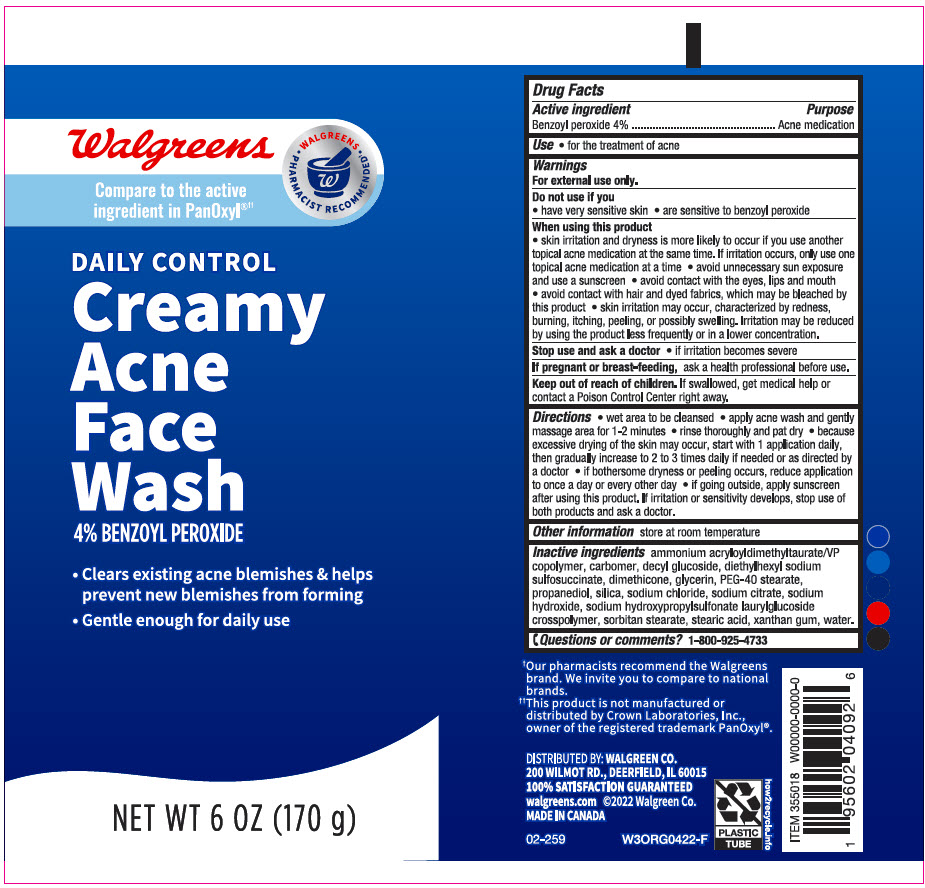 DRUG LABEL: Walgreens Creamy Acne Face Wash
NDC: 0363-2492 | Form: LOTION
Manufacturer: Walgreen Company
Category: otc | Type: HUMAN OTC DRUG LABEL
Date: 20240509

ACTIVE INGREDIENTS: Benzoyl Peroxide 40 mg/1 g
INACTIVE INGREDIENTS: AMMONIUM ACRYLOYLDIMETHYLTAURATE/VP COPOLYMER; CARBOMER HOMOPOLYMER, UNSPECIFIED TYPE; Decyl Glucoside; DOCUSATE SODIUM; Dimethicone; Glycerin; PEG-40 MONOSTEARATE; Propanediol; SILICON DIOXIDE; Sodium Chloride; Sodium Citrate, Unspecified Form; Sodium Hydroxide; SODIUM HYDROXYPROPYLSULFONATE LAURYLGLUCOSIDE-7 CROSSPOLYMER; SORBITAN MONOSTEARATE; Stearic Acid; Xanthan Gum; Water

Walgreens Creamy Acne Face Wash
Acne Medication

Drug Facts

Active ingredient

Benzoyl Peroxide 4%

Purpose

Acne medication

Use

- for the treatment of acne

Warnings

For external use only.

Do not use if you

- have very sensitive
- are sensitive to benzoyl peroxide

When using this product

- skin irritation and dryness are more likely to occur if you use another topical acne medication at the same time. If irritation occurs, only use one topical acne medication at a time
- avoid unnecessary sun exposure and use a sunscreen
- avoid contact with the eyes, lips and mouth
- avoid contact with hair and dyed fabrics, which may be bleached by this product
- skin irritation may occur, characterized by redness, burning, itching, peeling, or possibly swelling. Irritation may be reduced by using the product less frequently or in a lower concentration.

Stop use and ask a doctor if

- irritation becomes severe

PREGNANCY OR BREAST FEEDING

If pregnant or breast-feeding, ask a health professional before use.

Keep out of reach of children. If swallowed, get medical help or contact a Poison Control Center right away.

Directions

- Wet area to be cleansed
- apply acne wash and gently massage area for 1-2 minutes
- rinse thoroughly and pat dry
- because excessive drying of the skin may occur, start with 1 application daily, then gradually increase to 2 to 3 times daily if needed or as directed by a doctor
- if bothersome dryness or peeling occurs, reduce application to once a day or every other day
- if going outside, apply sunscreen after using this product. If irritation or sensitivity develops, stop use of both products and ask a doctor.

Other information

Store at room temperature

Inactive ingredients

ammonium acryloyldmethyltaurate/VP copolymer, carbomer, decyl glucoside, diethylhexyl sodium sulfosuccinate, dimethicone, glycerin, PEG-40 stearate, propanediol, silica, sodium chloride, sodium citrate, sodium hydroxide, sodium hydroxypropylsulfonate laurylglucoside crosspolymer, sorbitan stearate, stearic acid, xanthan gum, water.

Questions or comments?

1-800-925-4733

DISTRIBUTED BY: WALGREEN CO.
200 WILMOT RD., DEERFIELD, IL 60015

PRINCIPAL DISPLAY PANEL - 170 g Tube Label

Walgreens

Compare to the active
ingredient in PanOxyl®††

• WALGREENS •
PHARMACIST RECOMMENDED†

DAILY CONTROL

Creamy
Acne
Face
Wash

4% BENZOYL PEROXIDE

- Clears existing acne blemishes & helps
  prevent new blemishes from forming
- Gentle enough for daily use

NET WT 6 OZ (170 g)